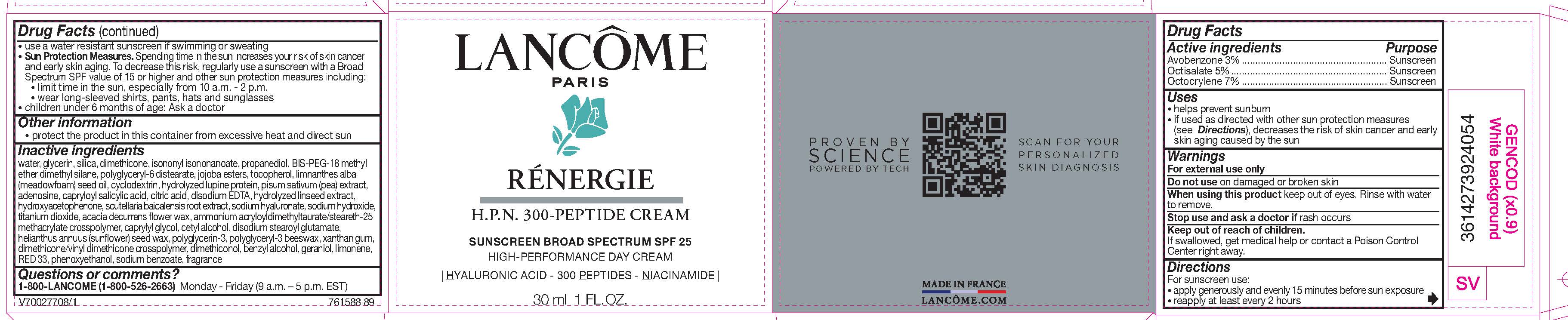 DRUG LABEL: Lancome Paris Renergie HPN 300 Peptide Broad Spectrum SPF 25 Sunscreen
NDC: 51150-240 | Form: CREAM
Manufacturer: SICOS ET CIE
Category: otc | Type: HUMAN OTC DRUG LABEL
Date: 20240626

ACTIVE INGREDIENTS: Avobenzone 30 mg/1 g; Octisalate 50 mg/1 g; Octocrylene 70 mg/1 g
INACTIVE INGREDIENTS: WATER; GLYCERIN; SILICON DIOXIDE; DIMETHICONE; ISONONYL ISONONANOATE; PROPANEDIOL; BIS-PEG-18 METHYL ETHER DIMETHYL SILANE; POLYGLYCERYL-6 DISTEARATE; HYDROLYZED JOJOBA ESTERS (ACID FORM); TOCOPHEROL; MEADOWFOAM SEED OIL; CYCLODEXTRINS; PEA; ADENOSINE; CAPRYLOYL SALICYLIC ACID; CITRIC ACID MONOHYDRATE; EDETATE DISODIUM; HYDROXYACETOPHENONE; SCUTELLARIA BAICALENSIS ROOT; HYALURONATE SODIUM; SODIUM HYDROXIDE; TITANIUM DIOXIDE; ACACIA DECURRENS FLOWER WAX; CAPRYLYL GLYCOL; CETYL ALCOHOL; DISODIUM STEAROYL GLUTAMATE; HELIANTHUS ANNUUS SEED WAX; POLYGLYCERIN-3; XANTHAN GUM; DIMETHICONE/VINYL DIMETHICONE CROSSPOLYMER (HARD PARTICLE); DIMETHICONOL (70 CST); BENZYL ALCOHOL; GERANIOL; LIMONENE, (+)-; D&C RED NO. 33; PHENOXYETHANOL; SODIUM BENZOATE

Drug Facts

Active ingredients

Avobenzone 3%

Octisalate 5%

Octocrylene 7%

Purpose

Sunscreen

Uses

- helps prevent sunburn
- if used as directed with other sun protection measures (see Directions), decreases the risk of skin cancer and early skin aging caused by the sun

Warnings

For external use only

Do not use

on damaged or broken skin

When using this product

keep out of eyes. Rinse with water to remove.

Stop use and ask a doctor if

rash occurs

Keep out of reach of children.

If swallowed, get medical help or contact a Poison Control Center right away.

Directions

For sunscreen use:
● apply generously and evenly 15 minutes before sun exposure
● reapply at least every 2 hours
● use a water resistant sunscreen if swimming or sweating
● Sun Protection Measures. Spending time in the sun increases your risk of skin cancer and early skin aging. To decrease this risk, regularly use a sunscreen with a Broad Spectrum SPF value of 15 or higher and other sun protection measures including:
● limit time in the sun, especially from 10 a.m. – 2 p.m.
● wear long-sleeved shirts, pants, hats, and sunglasses
● children under 6 months of age: Ask a doctor

Other information

- protect the product in this container from excessive heat and direct sun

Inactive ingredients

water, glycerin, silica, dimethicone, isononyl isononanoate, propanediol, bis-PEG-18 methyl ether dimethyl silane, polyglyceryl-6 distearate, jojoba esters, tocopherol, limnanthes alba (meadowfoam) seed oil, cyclodextrin, hydrolyzed lupine protein, pisum sativum (pea) extract, adenosine, capryloyl salicylic acid, citric acid, disodium EDTA, hydrolyzed linseed extract, hydroxyacetophenone, scutellaria baicalensis root extract, sodium hyaluronate, sodium hydroxide, titanium dioxide, acacia decurrens flower wax, ammonium acryloyldimethyltaurate/steareth-25 methacrylate crosspolymer, caprylyl glycol, cetyl alcohol, disodium stearoyl glutamate, helianthus annuus (sunflower) seed wax, polyglycerin-3, polyglyceryl-3 beeswax, xanthan gum, dimethicone/vinyl dimethicone crosspolymer, dimethiconol, benzyl alcohol, geraniol, limonene, red 33, phenoxyethanol, sodium benzoate, fragrance

Questions or comments?

1-800-LANCOME (1-800-526-2663) Monday - Friday (9 a.m. - 5 p.m. EST)